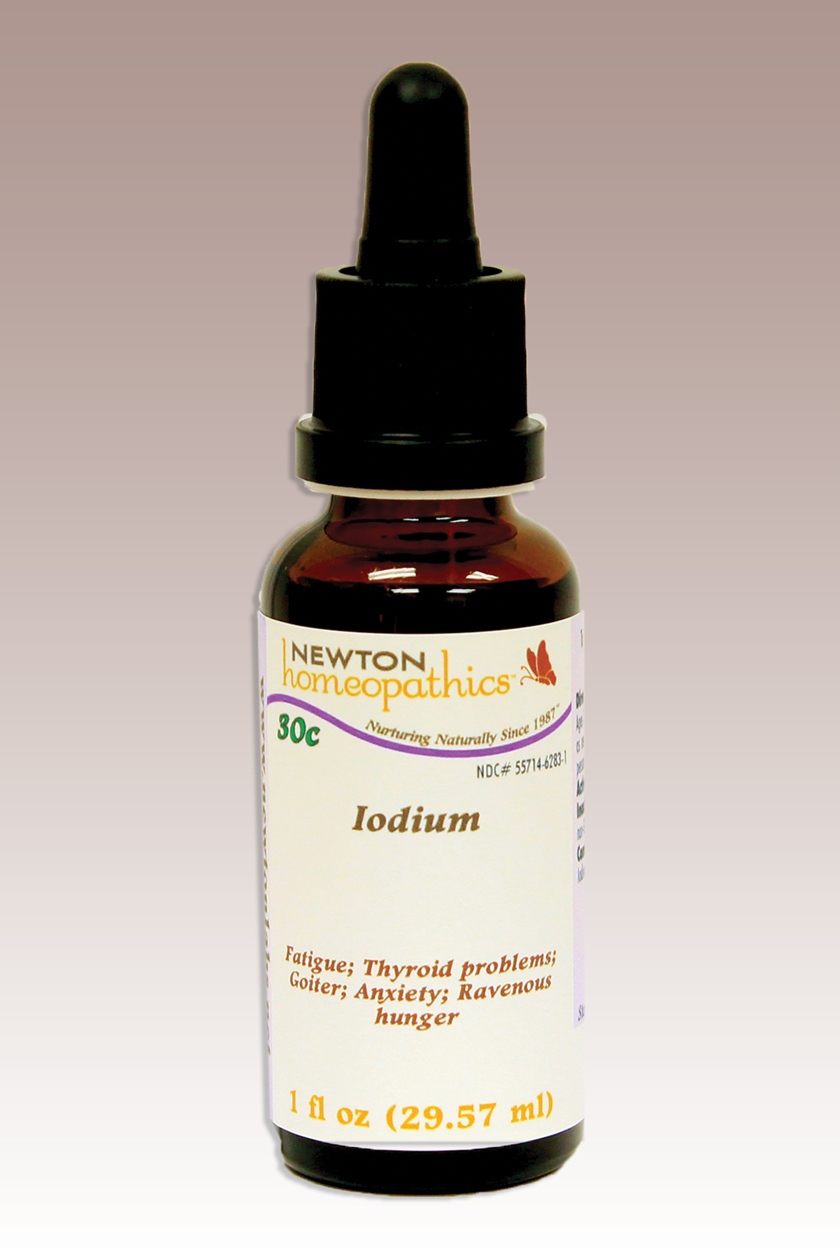 DRUG LABEL: Iodium 
NDC: 55714-6283 | Form: LIQUID
Manufacturer: Newton Laboratories, Inc.
Category: homeopathic | Type: HUMAN OTC DRUG LABEL
Date: 20110901

ACTIVE INGREDIENTS: Iodine 15 [hp_X]/1 mL
INACTIVE INGREDIENTS: Alcohol; Water

Iodine

INDICATIONS & USAGE SECTION

Fatigue, Thyroid problems, Goiter, Anxiety, Ravenous hunger.

DOSAGE & ADMINISTRATION SECTION

Directions: Ages 12 and up, take 6 drops by mouth (ages 0 to 11, give 3 drops) as needed or as directed by a health professional. Sensitive persons begin with 1 drop and gradually increase to full dose.

OTC - ACTIVE INGREDIENT SECTION

Iodium 15x, 10x, 200c, 30c.

OTC - PURPOSE SECTION

Fatigue, Thyroid problems, Goiter, Anxiety, Ravenous hunger.

INACTIVE INGREDIENT SECTION

Inactive Ingredients: USP Purified Water; USP Gluten-free, non-GMO, organic cane alcohol 20%.

QUESTIONS SECTION

www.newtonlabs.net Newton Laboratories, Inc. FDA Est # 1051203 - Conyers, GA 30012
Questions? 1.800.448.7256

WARNINGS SECTION

WARNINGS: Keep out of reach of children. Do not use if tamper-evident seal is broken or missing. If symptoms worsen or persist for more than a few days, consult a doctor. If pregnant or breast-feeding, ask a doctor before use.

OTC - PREGNANCY OR BREAST FEEDING SECTION

If pregnant or breast-feeding, ask a doctor before use.

OTC - KEEP OUT OF REACH OF CHILDREN SECTION

Keep out of reach of children.